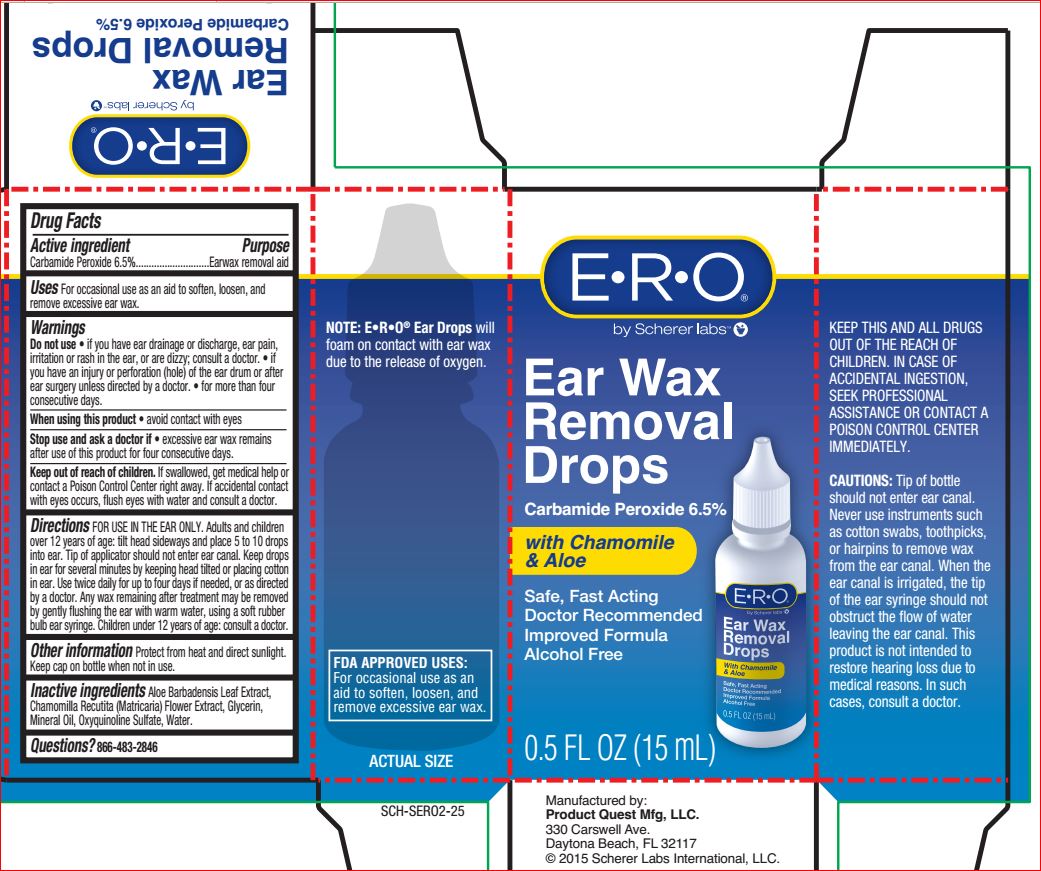 DRUG LABEL: Ear Wax Removal Drops
NDC: 64048-5118 | Form: LIQUID
Manufacturer: Product Quest Mfg
Category: otc | Type: HUMAN OTC DRUG LABEL
Date: 20180816

ACTIVE INGREDIENTS: Carbamide Peroxide 6.5 g/100 mL
INACTIVE INGREDIENTS: Aloe; CHAMOMILE; Glycerin; Mineral Oil; Oxyquinoline Sulfate; Water

Active ingredient Purpose
Carbamide Peroxide 6.5%............................Earwax removal aid

Uses

For occasional use as an aid to soften, loosen, and
remove excessive ear wax

Warnings
Do not use • if you have ear drainage or discharge, ear pain,
irritation or rash in the ear, or are dizzy; consult a doctor. • if
you have an injury or perforation (hole) of the ear drum or after
ear surgery unless directed by a doctor. • for more than four
consecutive days.
When using this product • avoid contact with eyes
Stop use and ask a doctor if • excessive ear wax remains
after use of this product for four consecutive days

Keep out of reach of children. If swallowed, get medical help or
contact a Poison Control Center right away. If accidental contact
with eyes occurs, flush eyes with water and consult a doctor.

DOSAGE AND ADMINISTRATION

Directions FOR USE IN THE EAR ONLY. Adults and children
over 12 years of age: tilt head sideways and place 5 to 10 drops
into ear. Tip of applicator should not enter ear canal. Keep drops
in ear for several minutes by keeping head tilted or placing cotton
in ear. Use twice daily for up to four days if needed, or as directed
by a doctor. Any wax remaining after treatment may be removed
by gently flushing the ear with warm water, using a soft rubber
bulb ear syringe. Children under 12 years of age: consult a doctor

Other information

Protect from heat and direct sunlight.
Keep cap on bottle when not in use

Inactive ingredients

Aloe Barbadensis Leaf Extract,
Chamomilla Recutita (Matricaria) Flower Extract, Glycerin,
Mineral Oil, Oxyquinoline Sulfate, Water.